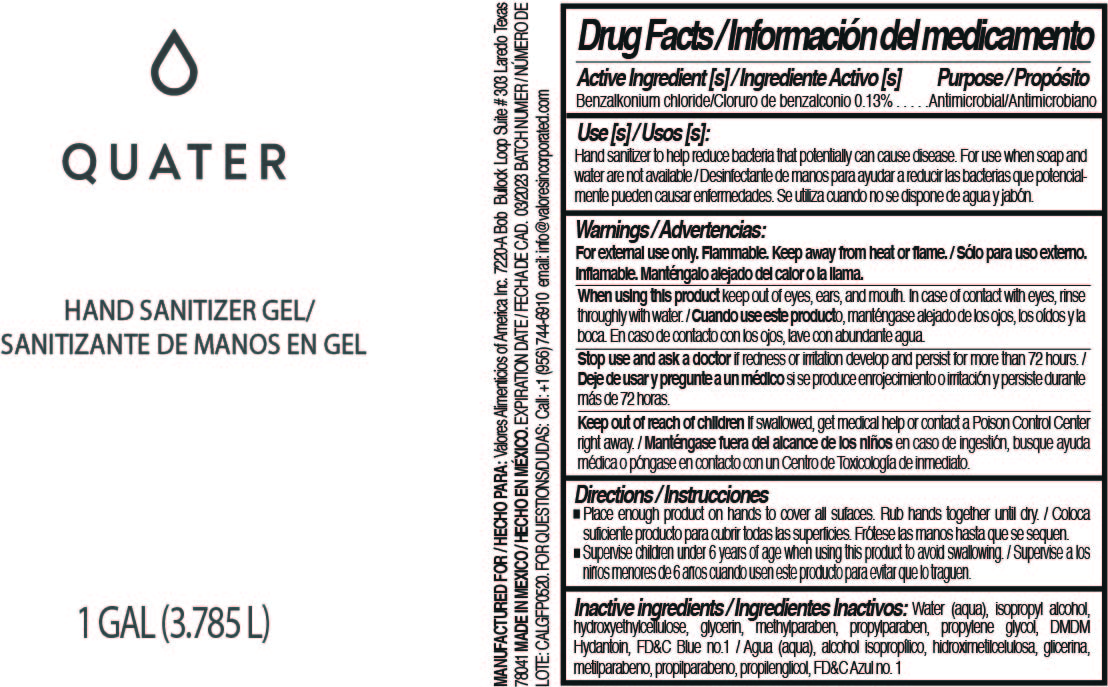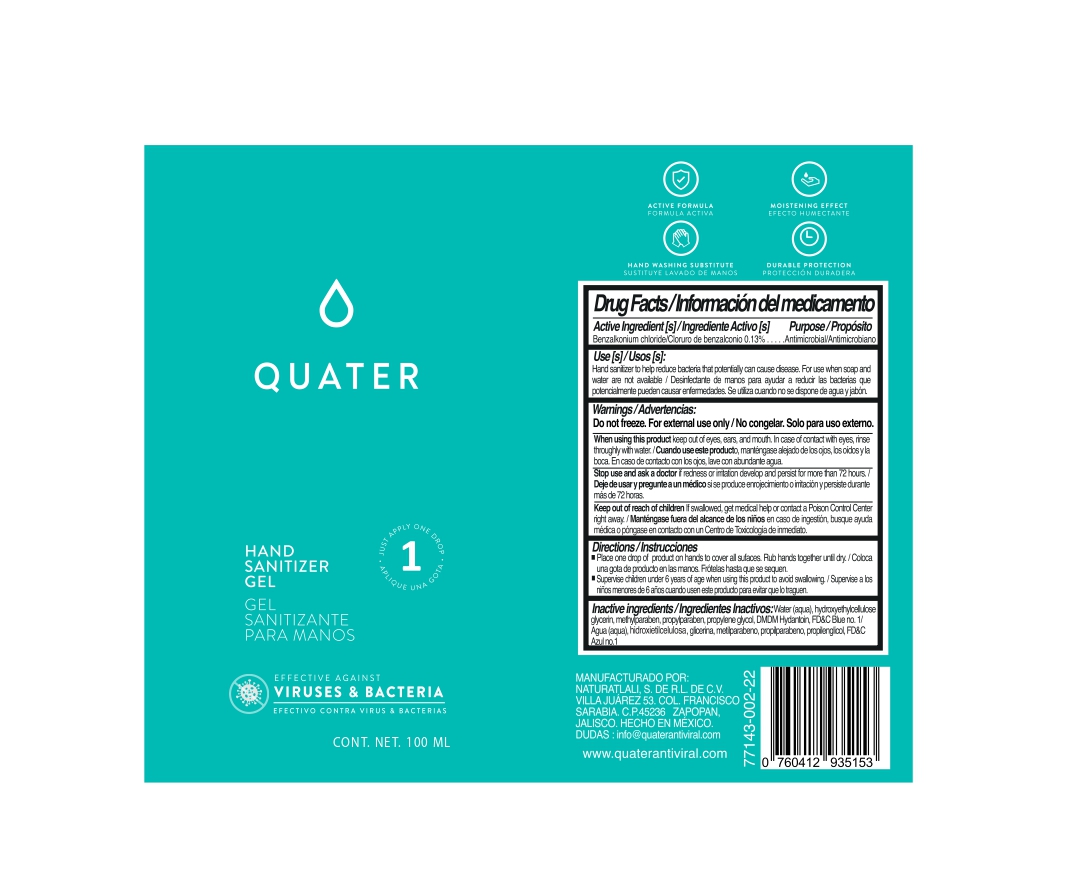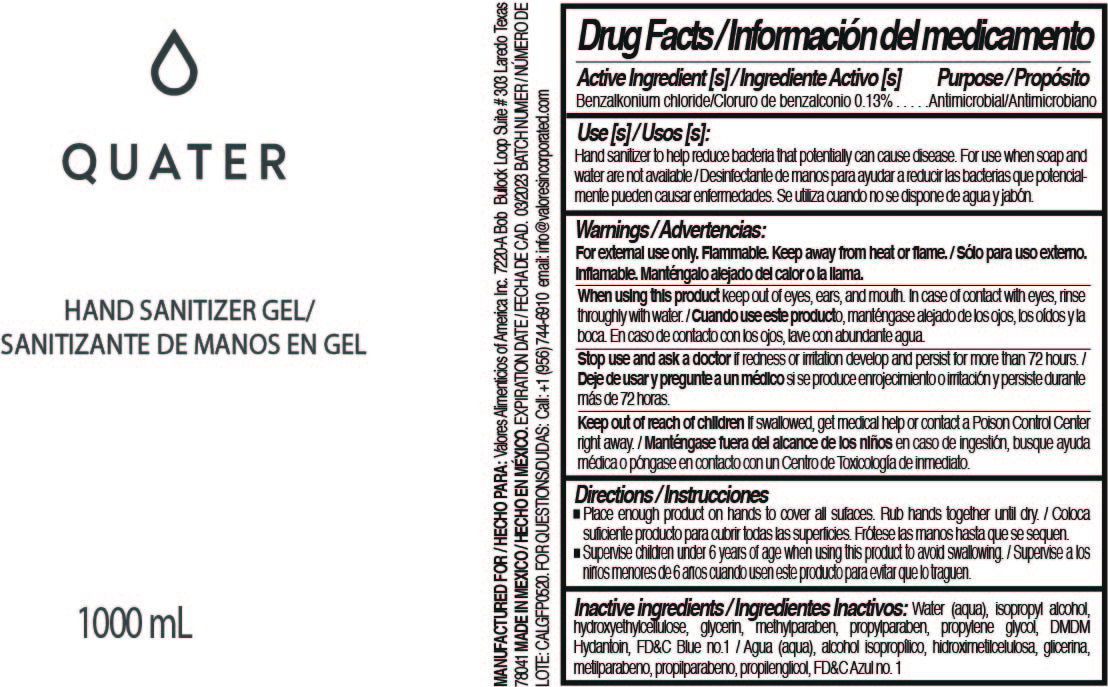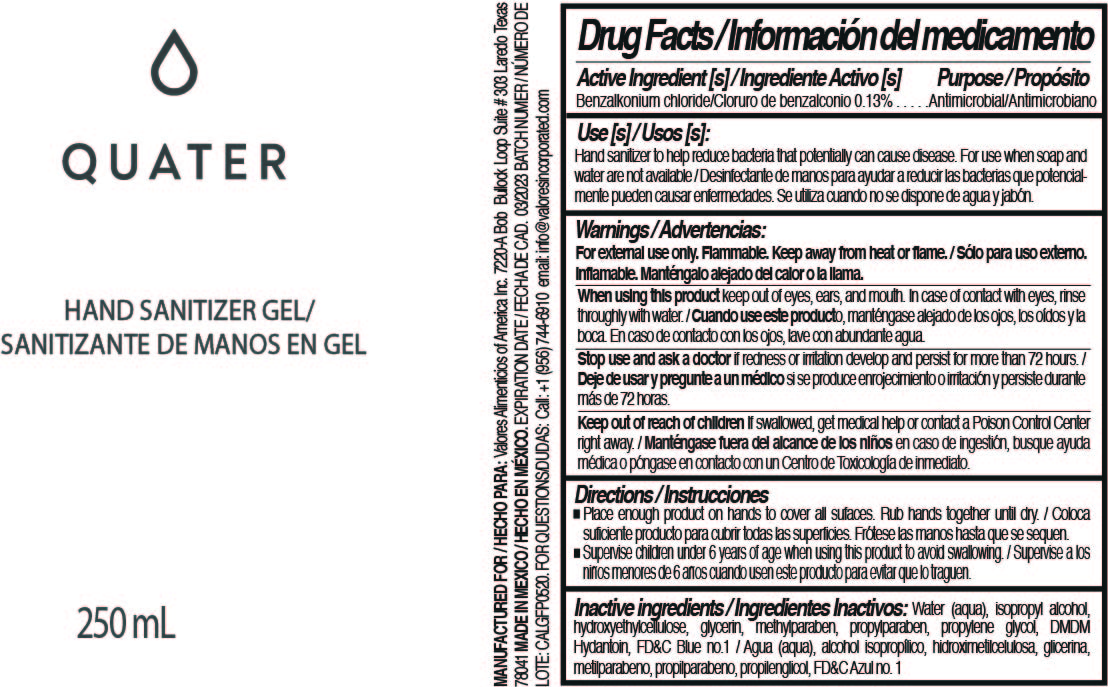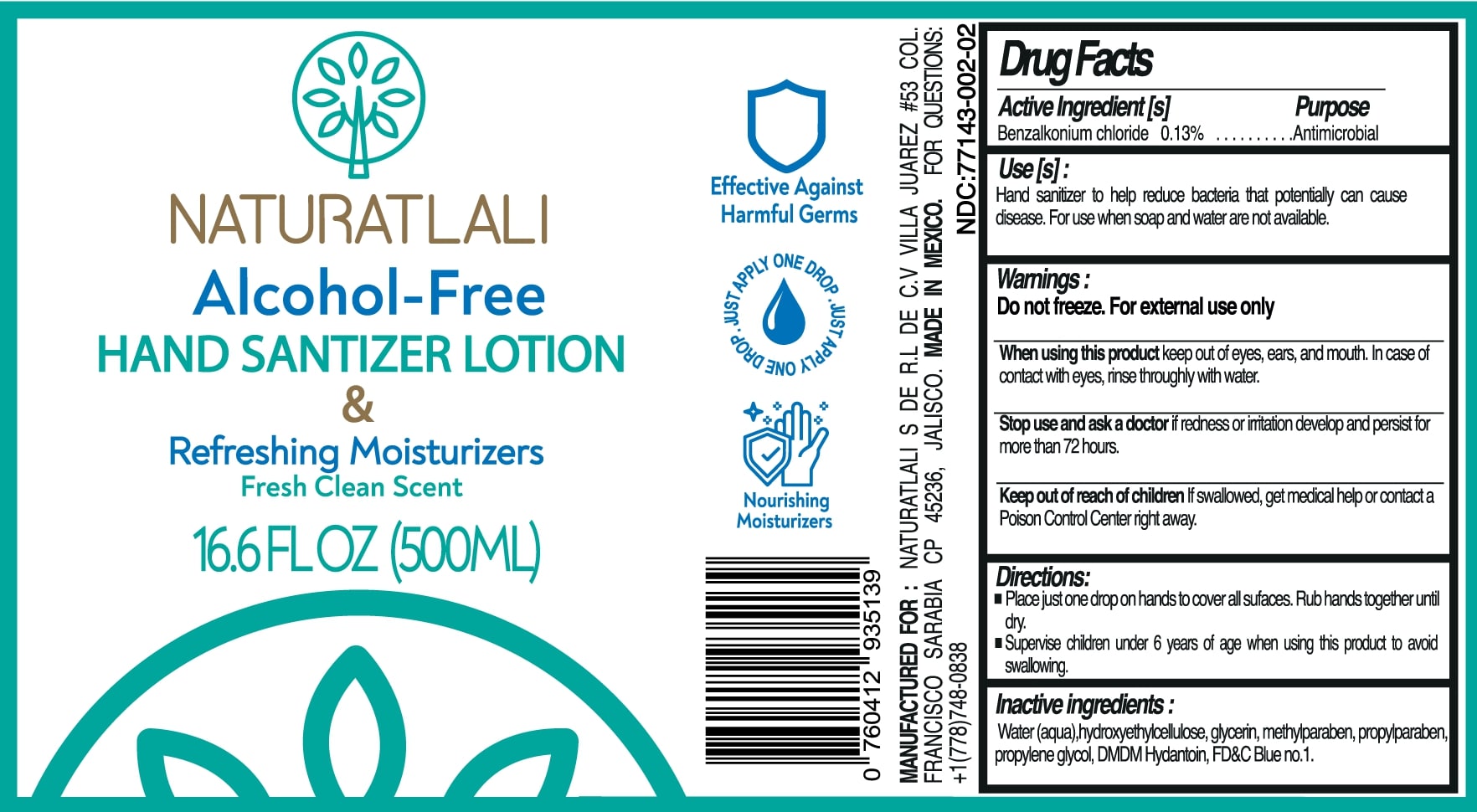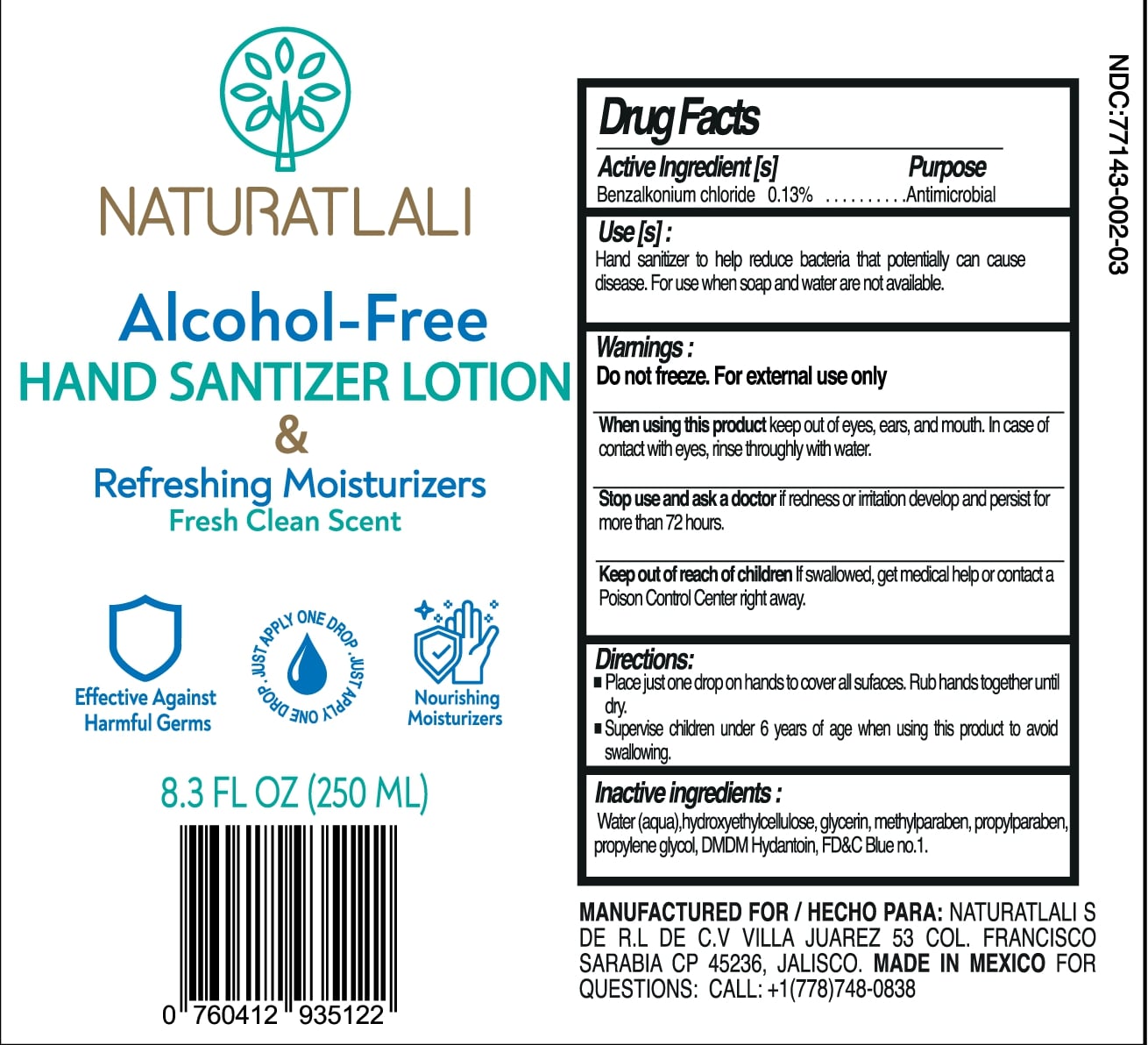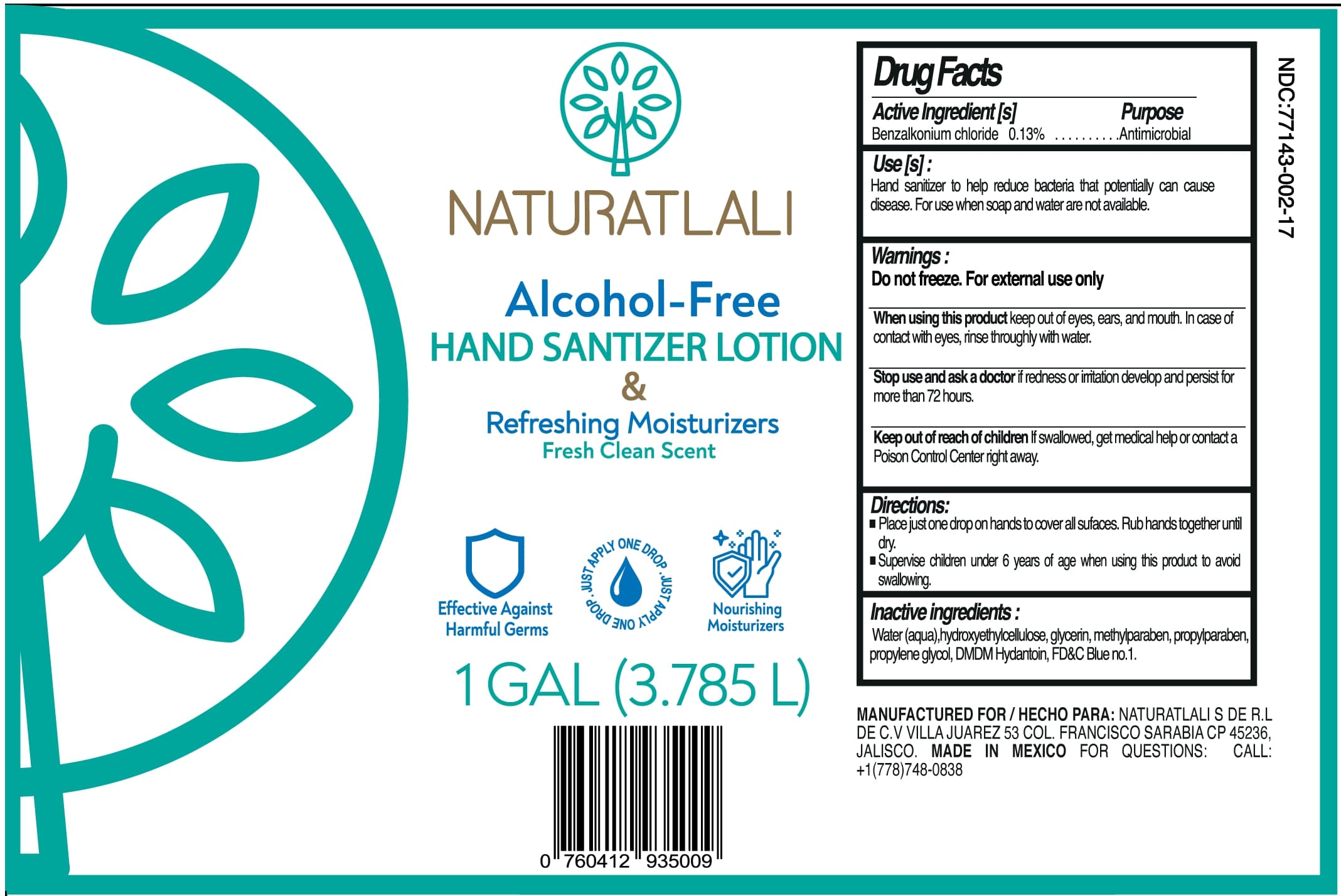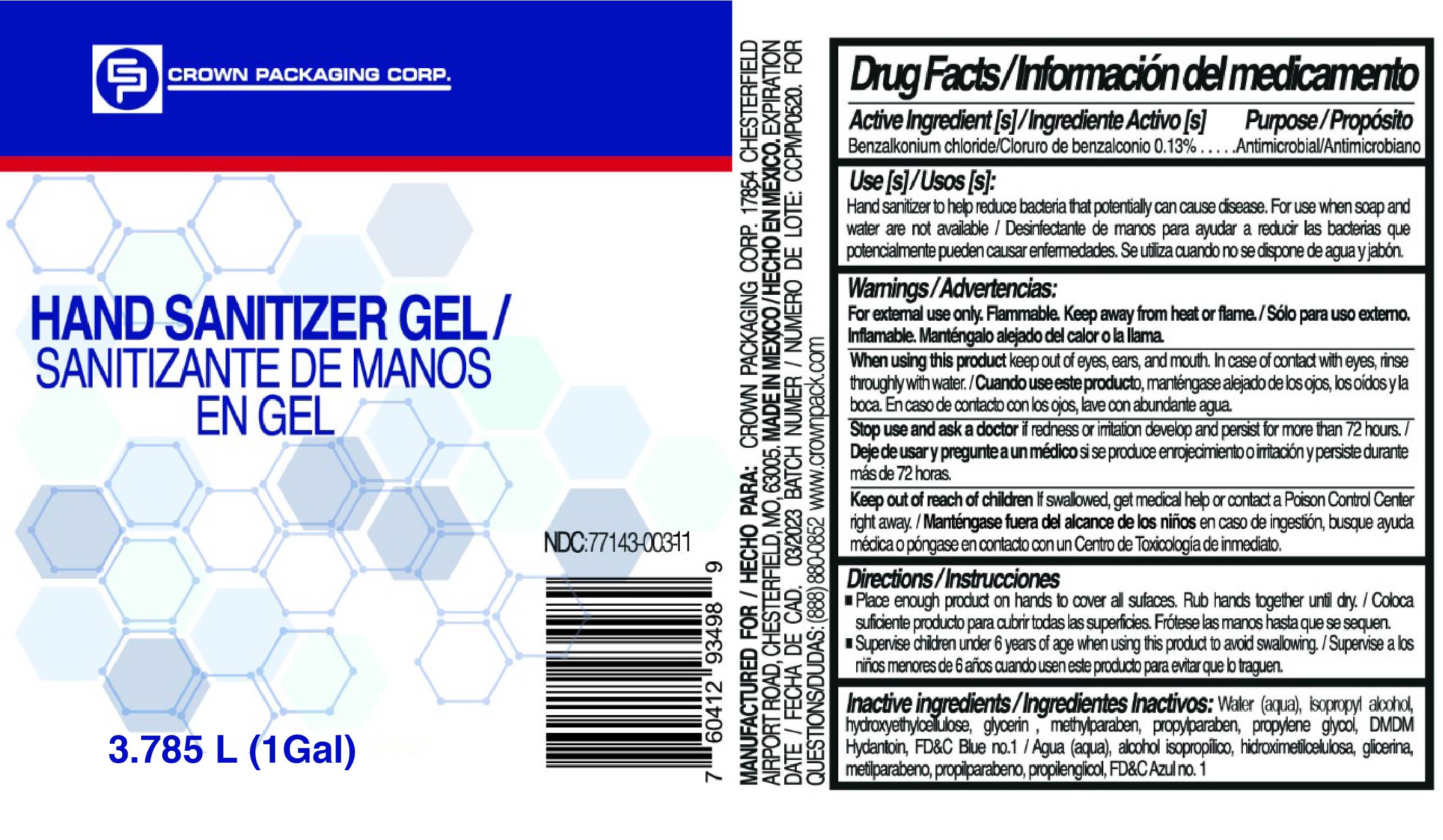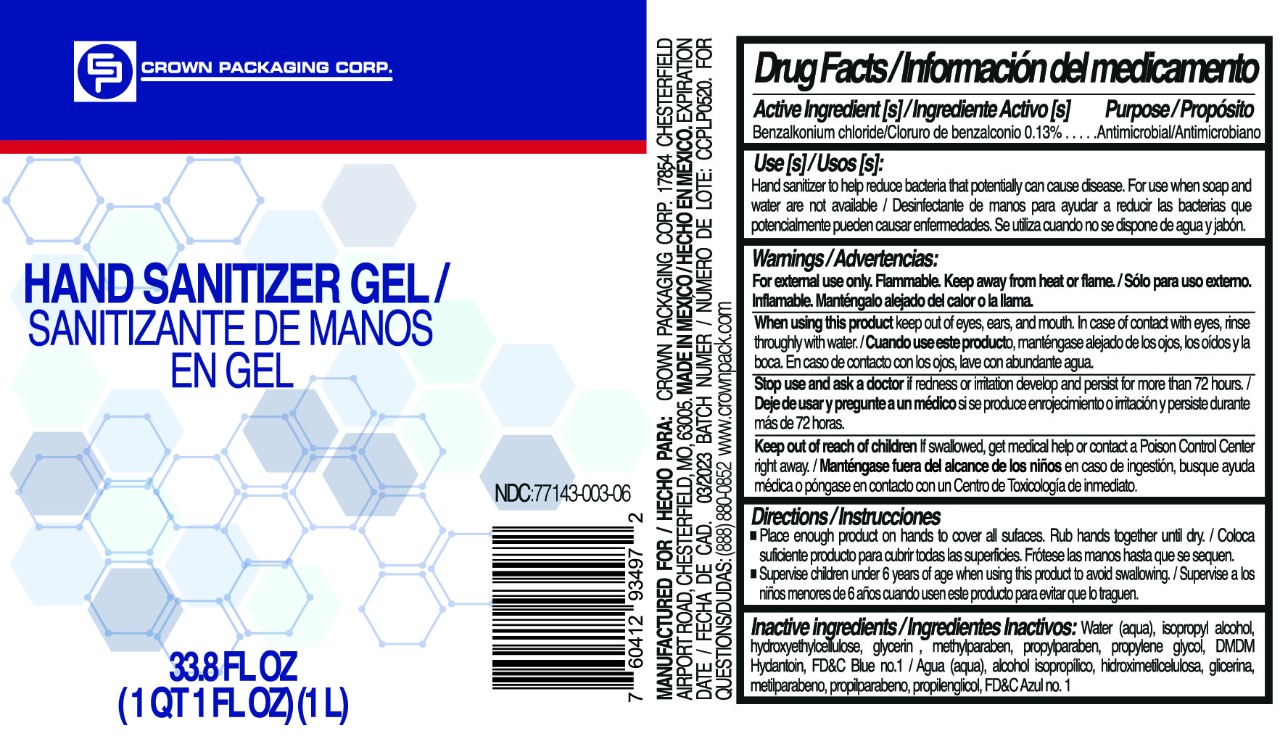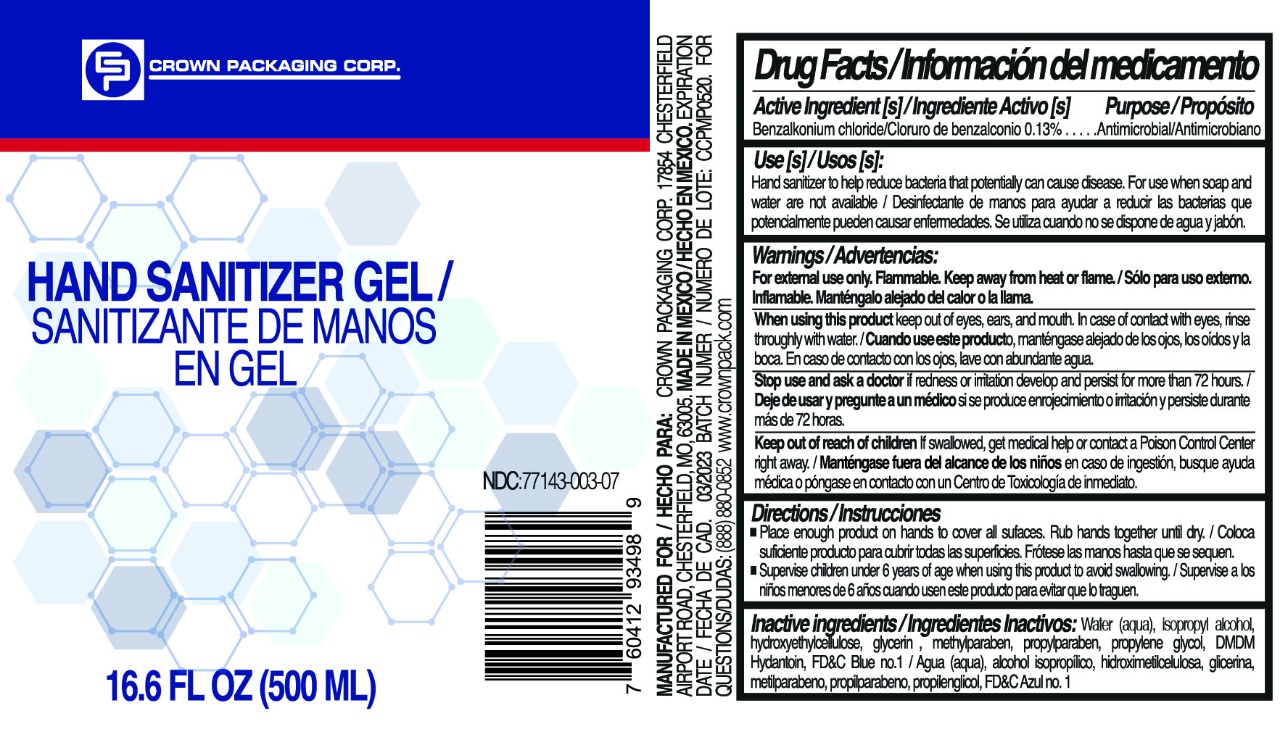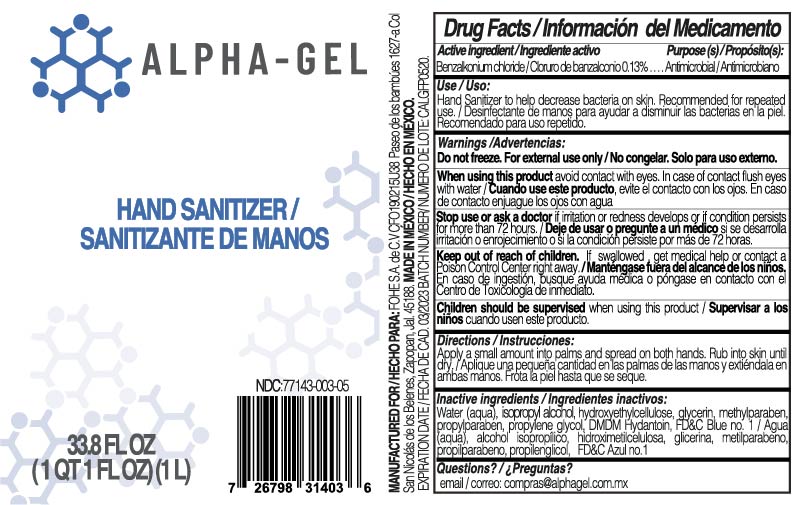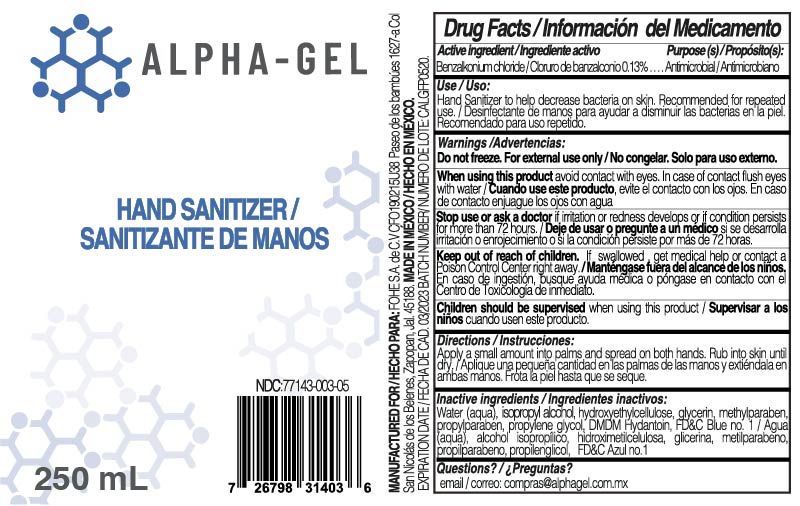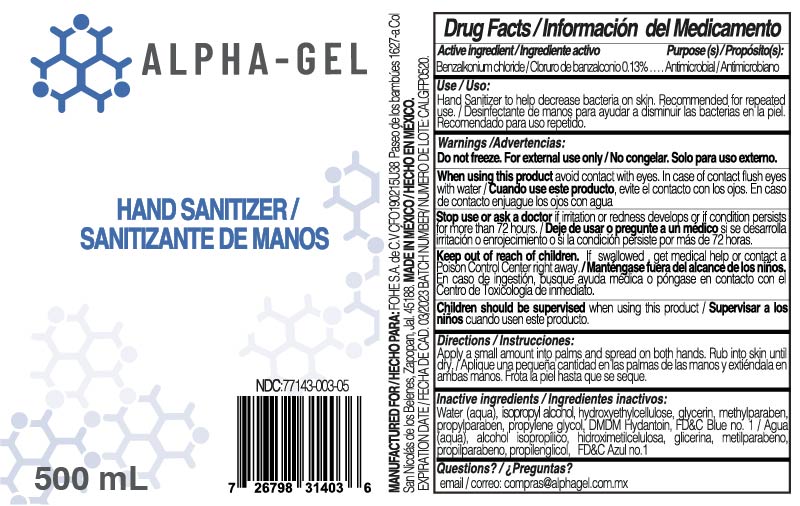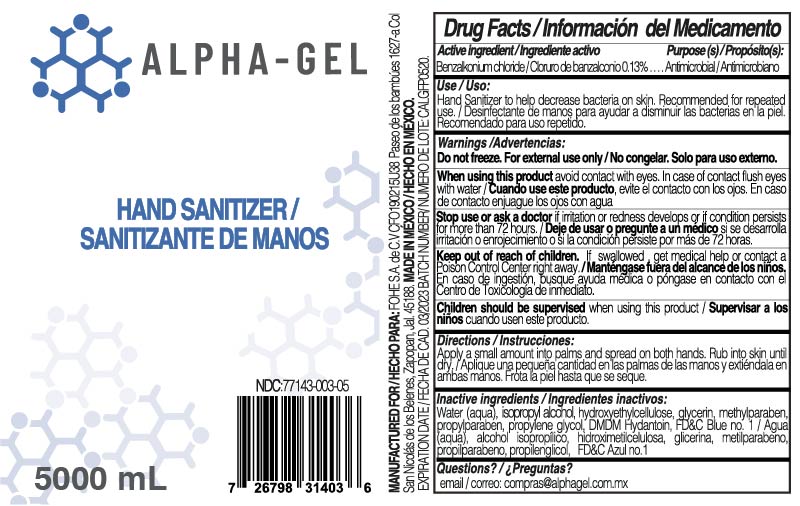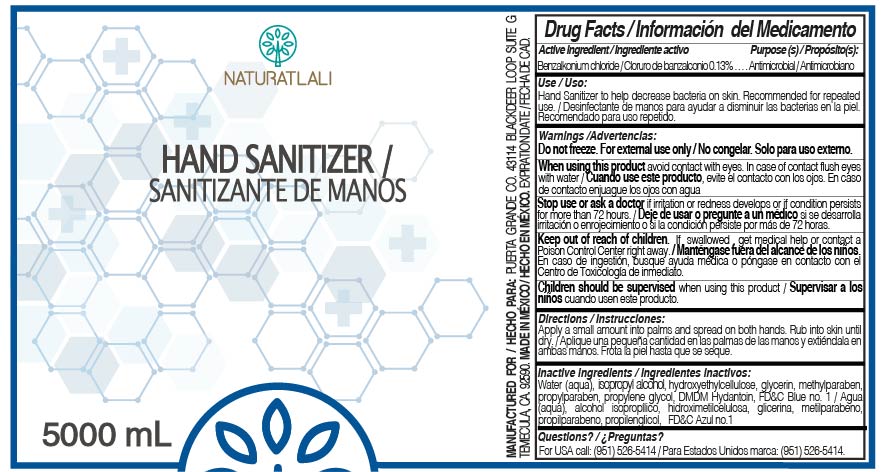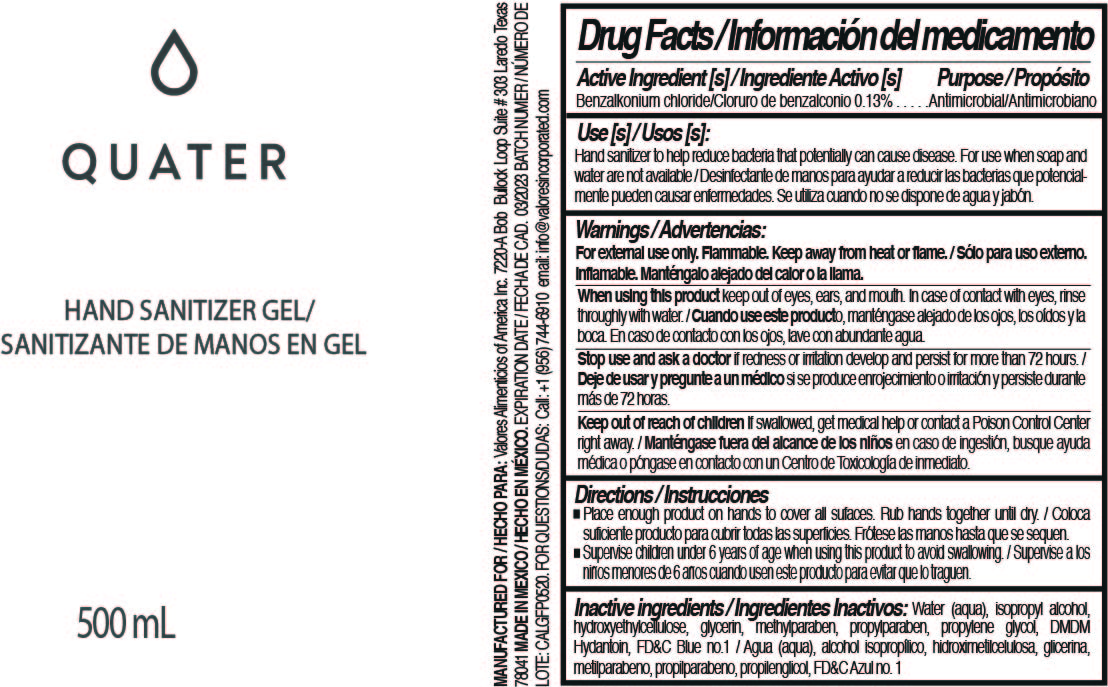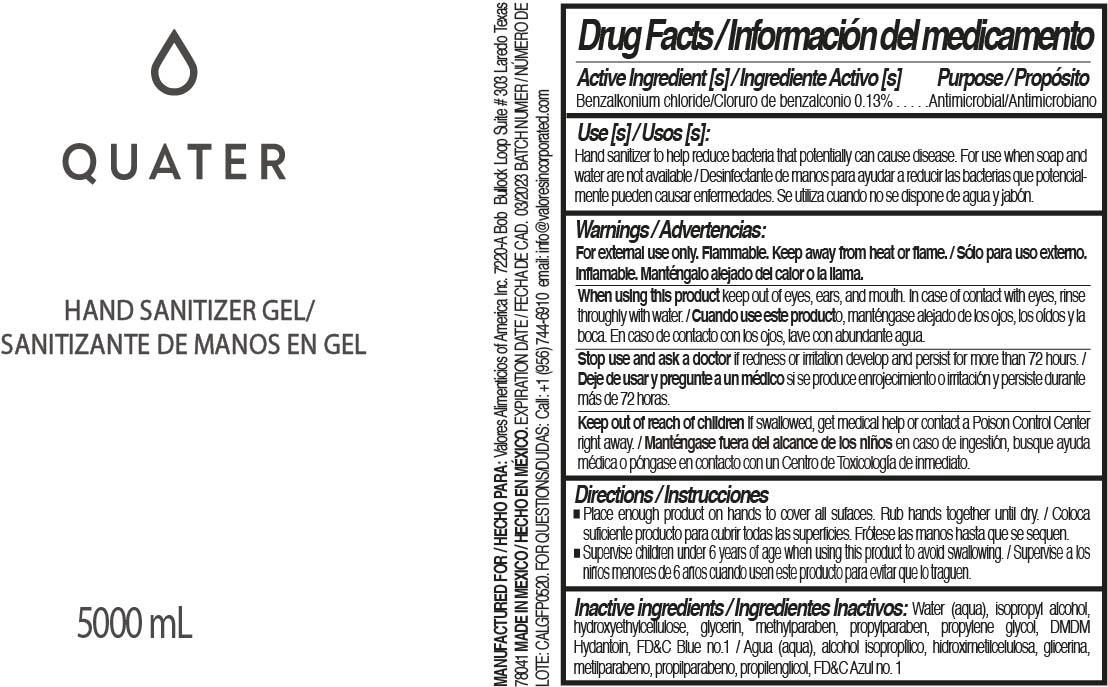 DRUG LABEL: Hand Sanitizer
NDC: 77143-002 | Form: GEL
Manufacturer: NATURATLALI S DE RL DE CV
Category: otc | Type: HUMAN OTC DRUG LABEL
Date: 20210223

ACTIVE INGREDIENTS: BENZALKONIUM CHLORIDE 0.13 g/100 mL
INACTIVE INGREDIENTS: GLYCERIN 0.25 mL/100 mL; HYDROXYETHYL CELLULOSE (100 MPA.S AT 2%) 0.1 g/100 mL; WATER; METHYLPARABEN 0.025 g/100 mL; PROPYLPARABEN 0.025 g/100 mL; DMDM HYDANTOIN 0.025 g/100 mL; FD&C BLUE NO. 1 0.005 g/100 mL; DIPROPYLENE GLYCOL 0.025 mL/100 mL

77143-002
Benzalkonium Chloride, Alcohol Free

Active Ingredient(s)

Benzalkonium Chloride 0.13% w/v. Purpose: Antiseptic

Purpose

Antiseptic, Hand Sanitizer

Use

Hand Sanitizer to help reduce bacteria that potentially can cause disease. For use when soap and water are not available.

Warnings

For external use only.

Do not use

- on open wounds

When using this product keep out of eyes, ears, and mouth. In case of contact with eyes, rinse eyes thoroughly with water.
Stop use and ask a doctor if irritation or rash occurs. These may be signs of a serious condition.
Keep out of reach of children. If swallowed, get medical help or contact a Poison Control Center right away.

Stop use and ask a doctor if irritation or rash occurs. These may be signs of a serious condition.

Keep out of reach of children. If swallowed, get medical help or contact a Poison Control Center right away.

Directions

- Place enough product on hands to cover all surfaces. Rub hands together until dry.
- Supervise children under 6 years of age when using this product to avoid swallowing.

Other information

- Store between 15-30C (59-86F)
- Avoid freezing and excessive heat above 40C (104F)

Inactive ingredients

water, hydroxyethylcellulose, glycerin, methylparaben, propylparaben, propylene glycol, DMDM Hydantoin, FD&C Blue No 1

Package Label - Principal Display Panel

500 mL NDC: 77143-002-02

250 mL NDC: 77143-002-03

5000 mL NDC: 77143-002-04

1000 mL NDC: 77143-002-05

1000 mL NDC: 77143-002-06

500 mL NDC: 77143-002-07

500 mL NDC: 77143-002-08

250 mL NDC: 77143-003-09

5000 mL NDC: 77143-002-10

3785 mL NDC: 77143-002-11

5000 mL NDC: 77143-002-12

250 mL NDC: 77143-002-13

500 mL NDC: 77143-002-14

1000 mL NDC: 77143-002-15

3785 mL NDC: 77143-002-16

3785 mL NDC: 77143-002-17

100 mL NDC: 77143-002-22